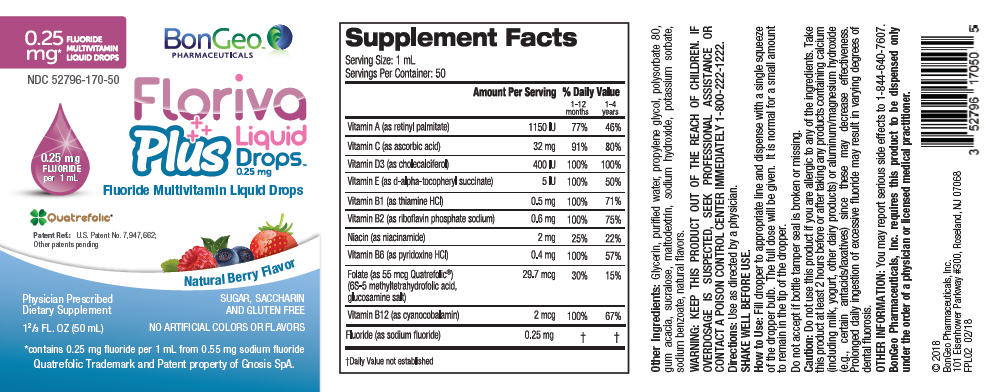 DRUG LABEL: Floriva Plus
NDC: 52796-170 | Form: SOLUTION/ DROPS
Manufacturer: BonGeo Pharmaceuticals, Inc.
Category: other | Type: DIETARY SUPPLEMENT
Date: 20180404

ACTIVE INGREDIENTS: VITAMIN A PALMITATE 1150 [iU]/1 mL; ASCORBIC ACID 32 mg/1 mL; CHOLECALCIFEROL 400 [iU]/1 mL; .ALPHA.-TOCOPHEROL SUCCINATE, D- 5 [iU]/1 mL; THIAMINE HYDROCHLORIDE 0.5 mg/1 mL; RIBOFLAVIN 5'-PHOSPHATE SODIUM 0.6 mg/1 mL; NIACINAMIDE 2 mg/1 mL; PYRIDOXINE HYDROCHLORIDE 0.4 mg/1 mL; LEVOMEFOLATE GLUCOSAMINE 29.7 ug/1 mL; CYANOCOBALAMIN 2 ug/1 mL; SODIUM FLUORIDE 0.25 mg/1 mL
INACTIVE INGREDIENTS: GLYCERIN; WATER; PROPYLENE GLYCOL; POLYSORBATE 80; ACACIA; SUCRALOSE; MALTODEXTRIN; SODIUM HYDROXIDE; POTASSIUM SORBATE; SODIUM BENZOATE

Floriva Plus Liquid Drops™

STATEMENT OF IDENTITY

Supplement Facts
Dosage Size: 1 mL |  | Servings Per Container: 50
Amount per 1 mL Ingredient | Amount Per Serving | % Daily Value
Amount per 1 mL Ingredient | Amount Per Serving | 1-12 months | 1-4 years
Vitamin A (as retinyl palmitate) | 345 mcg RAE | 69% | 115%
Vitamin C (as ascorbic acid) | 32 mg | 64% | 213%
Vitamin D3 (as cholecalciferol) | 10 mcg (400 IU) | 100% | 67%
Vitamin E (as d-alpha-tocopheryl succinate) | 3.4 mg (5 IU) | 68% | 57%
Vitamin B1 (as thiamine HCl) | 0.5 mg | 167% | 100%
Vitamin B2 (as riboflavin phosphate sodium) | 0.6 mg | 150% | 120%
Niacin (as niacinamide) | 2 mg | 50% | 33%
Vitamin B6 (as pyridoxine HCl) | 0.4 mg | 133% | 80%
Folate (as 55 mcg Quatrefolic | 49.5 mcg DFE | 62% | 33%
(6S-5 methyl tetrahydrofolic acid, (29.7 mcg Folic Acid) glucosamine salt)
Vitamin B12 (as cyanocobalamin) | 2 mcg | 400% | 222%
Fluoride (as sodium fluoride) | 0.25 mg | [Daily Value not established.]

Other Ingredients: Glycerin, purified water, propylene glycol, polysorbate 80, gum acacia, sucralose, maltodextrin, sodium hydroxide, potassium sorbate, sodium benzoate, natural flavors.

WARNING

KEEP THIS PRODUCT OUT OF THE REACH OF CHILDREN. IF OVERDOSAGE IS SUSPECTED, SEEK PROFESSIONAL ASSISTANCE OR CONTACT A POISON CONTROL CENTER IMMEDIATELY 1-800-222-1222.

Directions

Use as directed by a physician.

SHAKE WELL BEFORE USE.

How to Use

Fill dropper to appropriate line and dispense with a single squeeze of the dropper bulb. The full dose will be given. It is normal for a small amount to remain in the tip of the dropper.

SAFE HANDLING WARNING

Do not accept if bottle tamper seal is broken or missing.

Caution

Do not use this product if you are allergic to any of the ingredients. Take this product at least 2 hours before or after taking any products containing calcium (including milk, yogurt, other dairy products) or aluminum/magnesium hydroxide (e.g., certain antacids/laxatives) since these may decrease effectiveness. Prolonged daily ingestion of excessive fluoride may result in varying degrees of dental fluorosis.

OTHER INFORMATION

You may report serious side effects to 1-844-640-7607.

HEALTH CLAIM

BonGeo Pharmaceuticals, Inc. requires this product to be dispensed only under the order of a physician or licensed medical practitioner.

© 2018
BonGeo Pharmaceuticals, Inc.
101 Eisenhower Parkway #300, Roseland, NJ
07068 FPL02 02/18

PRINCIPAL DISPLAY PANEL - 50 mL Container Label

0.25
mg*
FLUORIDE
MULTIVITAMIN
LIQUID DROPS

BonGeo™
PHARMACEUTICALS

NDC 52796-170-50

0.25 mg
FLUORIDE
per 1 mL

Floriva
Plus
Liquid
Drops™
0.25 mg

Fluoride Multivitamin Liquid Drops

Quatrefolic®
Patent Ref.: U.S. Patent No. 7,947,662;
Other patents pending

Natural Berry Flavor

Physician Prescribed
Dietary Supplement

1⅔ FL. OZ (50 mL)

SUGAR, SACCHARIN
AND GLUTEN FREE

NO ARTIFICIAL COLORS OR FLAVORS

*contains 0.25 mg fluoride per 1 mL from 0.55 mg sodium fluoride

Quatrefolic Trademark and Patent property of Gnosis SpA.